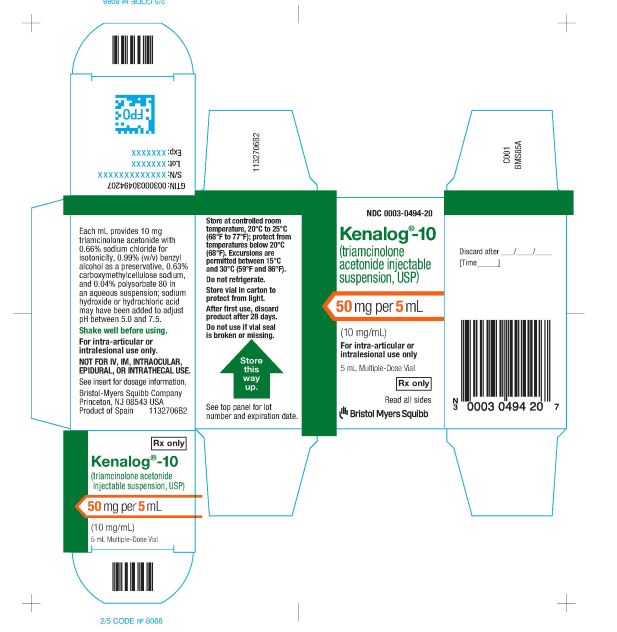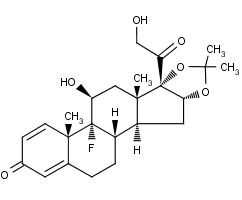 DRUG LABEL: KENALOG-10
NDC: 0003-0494 | Form: INJECTION, SUSPENSION
Manufacturer: E.R. Squibb & Sons, L.L.C.
Category: prescription | Type: HUMAN PRESCRIPTION DRUG LABEL
Date: 20240826

ACTIVE INGREDIENTS: triamcinolone acetonide 10 mg/1 mL
INACTIVE INGREDIENTS: sodium chloride; benzyl alcohol; polysorbate 80; sodium hydroxide; hydrochloric acid; nitrogen; CARBOXYMETHYLCELLULOSE SODIUM, UNSPECIFIED FORM

KENALOG®-10 INJECTION
(triamcinolone acetonide injectable suspension, USP)

NOT FOR USE IN NEONATES
CONTAINS BENZYL ALCOHOL

For Intra-articular or Intralesional Use Only

NOT FOR INTRAVENOUS, INTRAMUSCULAR, INTRAOCULAR, EPIDURAL, OR INTRATHECAL USE

DESCRIPTION

KENALOG®-10 Injection (triamcinolone acetonide injectable suspension, USP) is triamcinolone acetonide, a synthetic glucocorticoid corticosteroid with marked anti-inflammatory action, in a sterile aqueous suspension suitable for intralesional and intra-articular injection. THIS FORMULATION IS SUITABLE FOR INTRA-ARTICULAR AND INTRALESIONAL USE ONLY.

Each mL of the sterile aqueous suspension provides 10 mg triamcinolone acetonide, with 0.66% sodium chloride for isotonicity, 0.99% (w/v) benzyl alcohol as a preservative, 0.63% carboxymethylcellulose sodium, and 0.04% polysorbate 80. Sodium hydroxide or hydrochloric acid may have been added to adjust pH between 5.0 and 7.5. At the time of manufacture, the air in the container is replaced by nitrogen.

The chemical name for triamcinolone acetonide is 9-Fluoro-11β,16α,17,21-tetrahydroxypregna-1,4-diene-3,20-dione cyclic 16,17-acetal with acetone. Its structural formula is:

MW 434.50

CLINICAL PHARMACOLOGY

Glucocorticoids, naturally occurring and synthetic, are adrenocortical steroids that are readily absorbed from the gastrointestinal tract.

Naturally occurring glucocorticoids (hydrocortisone and cortisone), which also have salt-retaining properties, are used as replacement therapy in adrenocortical deficiency states. Synthetic analogs such as triamcinolone are primarily used for their anti-inflammatory effects in disorders of many organ systems.

INDICATIONS AND USAGE

The intra-articular or soft tissue administration of KENALOG-10 Injection (triamcinolone acetonide injectable suspension, USP) is indicated as adjunctive therapy for short-term administration (to tide the patient over an acute episode or exacerbation) in acute gouty arthritis, acute and subacute bursitis, acute nonspecific tenosynovitis, epicondylitis, rheumatoid arthritis, synovitis of osteoarthritis.

The intralesional administration of KENALOG-10 Injection is indicated for alopecia areata; discoid lupus erythematosus; keloids; localized hypertrophic, infiltrated, inflammatory lesions of granuloma annulare, lichen planus, lichen simplex chronicus (neurodermatitis), and psoriatic plaques; necrobiosis lipoidica diabeticorum.KENALOG-10 Injection may also be useful in cystic tumors of an aponeurosis or tendon (ganglia).

CONTRAINDICATIONS

KENALOG-10 Injection is contraindicated in patients who are hypersensitive to any components of this product (see WARNINGS: General).

Intramuscular corticosteroid preparations are contraindicated for idiopathic thrombocytopenic purpura.

WARNINGS

Serious Neurologic Adverse Reactions with Epidural Administration

Serious neurologic events, some resulting in death, have been reported with epidural injection of corticosteroids (see WARNINGS: Neurologic). Specific events reported include, but are not limited to, spinal cord infarction, paraplegia, quadriplegia, cortical blindness, and stroke. These serious neurologic events have been reported with and without use of fluoroscopy. The safety and effectiveness of epidural administration of corticosteroids have not been established, and corticosteroids are not approved for this use.

General

Exposure to excessive amounts of benzyl alcohol has been associated with toxicity (hypotension, metabolic acidosis), particularly in neonates, and an increased incidence of kernicterus, particularly in small preterm infants. There have been rare reports of deaths, primarily in preterm infants, associated with exposure to excessive amounts of benzyl alcohol. The amount of benzyl alcohol from medications is usually considered negligible compared to that received in flush solutions containing benzyl alcohol. Administration of high dosages of medications containing this preservative must take into account the total amount of benzyl alcohol administered. The amount of benzyl alcohol at which toxicity may occur is not known. If the patient requires more than the recommended dosages or other medications containing this preservative, the practitioner must consider the daily metabolic load of benzyl alcohol from these combined sources (see PRECAUTIONS: Pediatric Use).

Because KENALOG-10 Injection (triamcinolone acetonide injectable suspension, USP) is a suspension, it should not be administered intravenously. Strict aseptic technique is mandatory.

Rare instances of anaphylaxis have occurred in patients receiving corticosteroid therapy (see ADVERSE REACTIONS). Cases of serious anaphylaxis, including death, have been reported in individuals receiving triamcinolone acetonide injection, regardless of the route of administration.

Increased dosage of rapidly acting corticosteroids is indicated in patients on corticosteroid therapy subjected to any unusual stress before, during, and after the stressful situation.

KENALOG-10 Injection is a long-acting preparation, and is not suitable for use in acute stress situations.

Results from one multicenter, randomized, placebo-controlled study with methylprednisolone hemisuccinate, an intravenous corticosteroid, showed an increase in early (at 2 weeks) and late (at 6 months) mortality in patients with cranial trauma who were determined not to have other clear indications for corticosteroid treatment. High doses of systemic corticosteroids, including KENALOG-10 Injection, should not be used for the treatment of traumatic brain injury.

Cardio-Renal

Average and large doses of corticosteroids can cause elevation of blood pressure, salt and water retention, and increased excretion of potassium. These effects are less likely to occur with the synthetic derivatives except when they are used in large doses. Dietary salt restriction and potassium supplementation may be necessary. All corticosteroids increase calcium excretion.

Literature reports suggest an apparent association between use of corticosteroids and left ventricular free wall rupture after a recent myocardial infarction; therefore, therapy with corticosteroids should be used with great caution in these patients.

There have been cases reported in which concomitant use of amphotericin B and hydrocortisone was followed by cardiac enlargement and congestive heart failure (see PRECAUTIONS: Drug Interactions: Amphotericin B injection and potassium-depleting agents).

Endocrine

Corticosteroids can produce reversible hypothalamic-pituitary adrenal (HPA) axis suppression with the potential for glucocorticosteroid insufficiency after withdrawal of treatment.

Metabolic clearance of corticosteroids is decreased in hypothyroid patients and increased in hyperthyroid patients. Changes in thyroid status of the patient may necessitate adjustment in dosage.

Immunosuppression and Increased Risk of Infection

Corticosteroids, including KENALOG-10, suppress the immune system and increase the risk of infection with any pathogen, including viral, bacterial, fungal, protozoan, or helminthic pathogens. Corticosteroids can:
• Reduce resistance to new infections
• Exacerbate existing infections
• Increase the risk of disseminated infections
• Increase the risk of reactivation or exacerbation of latent infections
• Mask some signs of infection

Corticosteroid-associated infections can be mild but can be severe and at times fatal. The rate of infectious complications increases with increasing corticosteroid dosages.

Monitor for the development of infection and consider KENALOG-10 withdrawal or dosage reduction as needed.

Do not administer KENALOG-10 by an intraarticular, intrabursal, intratendinous or intralesional route in the presence of acute local infection.

Tuberculosis

If KENALOG-10 is used to treat a condition in patients with latent tuberculosis or tuberculin reactivity, reactivation of the disease may occur. Closely monitor such patients for reactivation. During prolonged KENALOG-10 therapy, patients with latent tuberculosis or tuberculin reactivity should receive chemoprophylaxis.

Varicella Zoster and Measles Viral Infections

Varicella and measles can have a serious or even fatal course in non-immune patients receiving corticosteroids, including KENALOG-10. In corticosteroid-treated patients who have not had these diseases or are non-immune, particular care should be taken to avoid exposure to varicella and measles:
• If a KENALOG-10-treated patient is exposed to varicella, prophylaxis with varicella zoster immune globulin (VZIG) may be indicated. If varicella develops, treatment with antiviral agents may be considered.
• If a KENALOG-10-treated patient is exposed to measles, prophylaxis with immunoglobulin (IG) may be indicated.

Hepatitis B virus reactivation can occur in patients who are hepatitis B carriers treated with immunosuppressive dosages of corticosteroids, including KENALOG-10. Reactivation can also occur infrequently in corticosteroid-treated patients who appear to have resolved hepatitis B infection.
Screen patients for hepatitis B infection before initiating immunosuppressive (e.g., prolonged) treatment with KENALOG-10. For patients who show evidence of hepatitis B infection, recommend consultation with physicians with expertise in managing hepatitis B regarding monitoring and consideration for hepatitis B antiviral therapy.

Fungal Infections

Corticosteroids, including KENALOG-10, may exacerbate systemic fungal infections; therefore, avoid KENALOG-10 use in the presence of such infections unless KENALOG-10 is needed to control drug reactions. For patients on chronic KENALOG-10 therapy who develop systemic fungal infections, KENALOG-10 withdrawal or dosage reduction is recommended.

Amebiasis

Corticosteroids, including KENALOG-10, may activate latent amebiasis. Therefore, it is recommended that latent amebiasis or active amebiasis be ruled out before initiating KENALOG-10 in patients who have spent time in the tropics or patients with unexplained diarrhea.

Strongyloides Infestation

Corticosteroids, including KENALOG-10, should be used with great care in patients with known or suspected Strongyloides (threadworm) infestation. In such patients, corticosteroid-induced immunosuppression may lead to Strongyloides hyperinfection and dissemination with widespread larval migration, often accompanied by severe enterocolitis and potentially fatal gram-negative septicemia.

Cerebral Malaria

Avoid corticosteroids, including KENALOG-10, in patients with cerebral malaria.

Vaccination

Administration of live or live, attenuated vaccines is contraindicated in patients receiving immunosuppressive doses of corticosteroids. Killed or inactivated vaccines may be administered. However, the response to such vaccines cannot be predicted. Immunization procedures may be undertaken in patients who are receiving corticosteroids as replacement therapy, e.g., for Addison’s disease.

Neurologic

Epidural and intrathecal administration of this product is not recommended. Reports of serious medical events, including death, have been associated with epidural and intrathecal routes of corticosteroid administration (see ADVERSE REACTIONS: Gastrointestinal and Neurologic/Psychiatric).

Ophthalmic

Use of corticosteroids may produce posterior subcapsular cataracts, glaucoma with possible damage to the optic nerves, and may enhance the establishment of secondary ocular infections due to bacteria, fungi, or viruses. The use of oral corticosteroids is not recommended in the treatment of optic neuritis and may lead to an increase in the risk of new episodes. Corticosteroids should not be used in active ocular herpes simplex.

Adequate studies to demonstrate the safety of KENALOG-10 Injection use by intraturbinal, subconjunctival, sub-Tenons, retrobulbar, and intraocular (intravitreal) injections have not been performed. Endophthalmitis, eye inflammation, increased intraocular pressure, and visual disturbances including vision loss have been reported with intravitreal administration. Administration of KENALOG-10 Injection intraocularly or into the nasal turbinates is not recommended.

Intraocular injection of corticosteroid formulations containing benzyl alcohol, such as KENALOG-10 Injection, is not recommended because of potential toxicity from the benzyl alcohol.

Kaposi’s sarcoma has been reported to occur in patients receiving corticosteroid therapy, most often for chronic conditions. Discontinuation of corticosteroids may result in clinical improvement of Kaposi’s sarcoma.

PRECAUTIONS

General

This product, like many other steroid formulations, is sensitive to heat. Therefore, it should not be autoclaved when it is desirable to sterilize the exterior of the vial.

The lowest possible dose of corticosteroid should be used to control the condition under treatment. When reduction in dosage is possible, the reduction should be gradual.

Since complications of treatment with glucocorticoids are dependent on the size of the dose and the duration of treatment, a risk/benefit decision must be made in each individual case as to dose and duration of treatment and as to whether daily or intermittent therapy should be used.

Cardio-Renal

As sodium retention with resultant edema and potassium loss may occur in patients receiving corticosteroids, these agents should be used with caution in patients with congestive heart failure, hypertension, or renal insufficiency.

Endocrine

Drug-induced secondary adrenocortical insufficiency may be minimized by gradual reduction of dosage. This type of relative insufficiency may persist for months after discontinuation of therapy; therefore, in any situation of stress occurring during that period, hormone therapy should be reinstituted. Since mineralocorticoid secretion may be impaired, salt and/or a mineralocorticoid should be administered concurrently.

Gastrointestinal

Steroids should be used with caution in active or latent peptic ulcers, diverticulitis, fresh intestinal anastomoses, and nonspecific ulcerative colitis, since they may increase the risk of a perforation.

Signs of peritoneal irritation following gastrointestinal perforation in patients receiving corticosteroids may be minimal or absent.

There is an enhanced effect of corticosteroids in patients with cirrhosis.

Intra-Articular and Soft Tissue Administration

Intra-articularly injected corticosteroids may be systemically absorbed.

Appropriate examination of any joint fluid present is necessary to exclude a septic process.

A marked increase in pain accompanied by local swelling, further restriction of joint motion, fever, and malaise are suggestive of septic arthritis. If this complication occurs and the diagnosis of sepsis is confirmed, appropriate antimicrobial therapy should be instituted.

Injection of a steroid into an infected site is to be avoided. Local injection of a steroid into a previously infected joint is not usually recommended.

Corticosteroid injection into unstable joints is generally not recommended.

Intra-articular injection may result in damage to joint tissues (see ADVERSE REACTIONS: Musculoskeletal).

Musculoskeletal

Corticosteroids decrease bone formation and increase bone resorption both through their effect on calcium regulation (i.e., decreasing absorption and increasing excretion) and inhibition of osteoblast function. This, together with a decrease in the protein matrix of the bone secondary to an increase in protein catabolism, and reduced sex hormone production, may lead to inhibition of bone growth in pediatric patients and the development of osteoporosis at any age. Special consideration should be given to patients at increased risk of osteoporosis (i.e., postmenopausal women) before initiating corticosteroid therapy.

Neuro-Psychiatric

Although controlled clinical trials have shown corticosteroids to be effective in speeding the resolution of acute exacerbations of multiple sclerosis, they do not show that they affect the ultimate outcome or natural history of the disease. The studies do show that relatively high doses of corticosteroids are necessary to demonstrate a significant effect. (See DOSAGE AND ADMINISTRATION).

An acute myopathy has been observed with the use of high doses of corticosteroids, most often occurring in patients with disorders of neuromuscular transmission (e.g., myasthenia gravis), or in patients receiving concomitant therapy with neuromuscular blocking drugs (e.g., pancuronium). This acute myopathy is generalized, may involve ocular and respiratory muscles, and may result in quadriparesis. Elevation of creatinine kinase may occur. Clinical improvement or recovery after stopping corticosteroids may require weeks to years.

Psychiatric derangements may appear when corticosteroids are used, ranging from euphoria, insomnia, mood swings, personality changes, and severe depression to frank psychotic manifestations. Also, existing emotional instability or psychotic tendencies may be aggravated by corticosteroids.

Ophthalmic

Intraocular pressure may become elevated in some individuals. If steroid therapy is continued for more than 6 weeks, intraocular pressure should be monitored.

Information for Patients

Patients should be warned not to discontinue the use of corticosteroids abruptly or without medical supervision, to advise any medical attendants that they are taking corticosteroids, and to seek medical advice at once should they develop fever or other signs of infection.

Persons who are on corticosteroids should be warned to avoid exposure to chicken pox or measles. Patients should also be advised that if they are exposed, medical advice should be sought without delay.

Drug Interactions

Aminoglutethimide: Aminoglutethimide may lead to a loss of corticosteroid-induced adrenal suppression.

Amphotericin B injection and potassium-depleting agents: When corticosteroids are administered concomitantly with potassium-depleting agents (i.e., amphotericin B, diuretics), patients should be observed closely for development of hypokalemia. There have been cases reported in which concomitant use of amphotericin B and hydrocortisone was followed by cardiac enlargement and congestive heart failure.

Antibiotics: Macrolide antibiotics have been reported to cause a significant decrease in corticosteroid clearance.

Anticholinesterases: Concomitant use of anticholinesterase agents and corticosteroids may produce severe weakness in patients with myasthenia gravis. If possible, anticholinesterase agents should be withdrawn at least 24 hours before initiating corticosteroid therapy.

Anticoagulants, oral: Coadministration of corticosteroids and warfarin usually results in inhibition of response to warfarin, although there have been some conflicting reports. Therefore, coagulation indices should be monitored frequently to maintain the desired anticoagulant effect.

Antidiabetics: Because corticosteroids may increase blood glucose concentrations, dosage adjustments of antidiabetic agents may be required.

Antitubercular drugs: Serum concentrations of isoniazid may be decreased.

Cholestyramine: Cholestyramine may increase the clearance of corticosteroids.

Cyclosporine: Increased activity of both cyclosporine and corticosteroids may occur when the two are used concurrently. Convulsions have been reported with this concurrent use.

CYP3A4 inhibitors: Triamcinolone acetonide is a substrate of CYP3A4. Ketoconazole has been reported to decrease the metabolism of certain corticosteroids by up to 60%, leading to an increased risk of corticosteroid side effects. Co-administration of other strong CYP3A4 inhibitors (e.g., ritonavir, atazanavir, clarithromycin, indinavir, itraconazole, nefazodone, nelfinavir, saquinavir, telithromycin, cobicistat-containing products) with KENALOG-10 Injection may cause increased plasma concentration of triamcinolone leading to adverse reactions. (See ADVERSE REACTIONS) During postmarketing use, there have been reports of clinically significant drug interactions in patients receiving triamcinolone acetonide and strong CYP3A4 inhibitors (e.g., ritonavir). (See WARNINGS, Endocrine and PRECAUTIONS, Endocrine) Consider the benefit-risk of concomitant use and monitor for systemic corticosteroid side effects.

Digitalis glycosides: Patients on digitalis glycosides may be at increased risk of arrhythmias due to hypokalemia.

Estrogens, including oral contraceptives: Estrogens may decrease the hepatic metabolism of certain corticosteroids, thereby increasing their effect.

Hepatic enzyme inducers (e.g., barbiturates, phenytoin, carbamazepine, rifampin): Drugs which induce hepatic microsomal drug metabolizing enzyme activity may enhance the metabolism of corticosteroids and require that the dosage of the corticosteroid be increased.

Nonsteroidal anti-inflammatory drugs (NSAIDs): Concomitant use of aspirin (or other nonsteroidal anti-inflammatory drugs) and corticosteroids increases the risk of gastrointestinal side effects. Aspirin should be used cautiously in conjunction with corticosteroids in hypoprothrombinemia. The clearance of salicylates may be increased with concurrent use of corticosteroids.

Skin tests: Corticosteroids may suppress reactions to skin tests.

Vaccines: Patients on prolonged corticosteroid therapy may exhibit a diminished response to toxoids and live or inactivated vaccines due to inhibition of antibody response. Corticosteroids may also potentiate the replication of some organisms contained in live attenuated vaccines. Routine administration of vaccines or toxoids should be deferred until corticosteroid therapy is discontinued if possible (see WARNINGS: Immunosuppression and Increased Risk of Infection, Vaccination).

Carcinogenesis, Mutagenesis, Impairment of Fertility

No adequate studies have been conducted in animals to determine whether corticosteroids have a potential for carcinogenesis or mutagenesis.

Steroids may increase or decrease motility and number of spermatozoa in some patients.

Pregnancy

Teratogenic Effects

Corticosteroids have been shown to be teratogenic in many species when given in doses equivalent to the human dose. Animal studies in which corticosteroids have been given to pregnant mice, rats, and rabbits have yielded an increased incidence of cleft palate in the offspring. There are no adequate and well-controlled studies in pregnant women. Corticosteroids should be used during pregnancy only if the potential benefit justifies the potential risk to the fetus. Infants born to mothers who have received corticosteroids during pregnancy should be carefully observed for signs of hypoadrenalism.

Nursing Mothers

Systemically administered corticosteroids appear in human milk and could suppress growth, interfere with endogenous corticosteroid production, or cause other untoward effects. Caution should be exercised when corticosteroids are administered to a nursing woman.

Pediatric Use

This product contains benzyl alcohol as a preservative. Benzyl alcohol, a component of this product, has been associated with serious adverse events and death, particularly in pediatric patients. The “gasping syndrome” (characterized by central nervous system depression, metabolic acidosis, gasping respirations, and high levels of benzyl alcohol and its metabolites found in the blood and urine) has been associated with benzyl alcohol dosages >99 mg/kg/day in neonates and low-birth-weight neonates. Additional symptoms may include gradual neurological deterioration, seizures, intracranial hemorrhage, hematologic abnormalities, skin breakdown, hepatic and renal failure, hypotension, bradycardia, and cardiovascular collapse. Although normal therapeutic doses of this product deliver amounts of benzyl alcohol that are substantially lower than those reported in association with the “gasping syndrome,” the minimum amount of benzyl alcohol at which toxicity may occur is not known. Premature and low-birth-weight infants, as well as patients receiving high dosages, may be more likely to develop toxicity. Practitioners administering this and other medications containing benzyl alcohol should consider the combined daily metabolic load of benzyl alcohol from all sources.

The efficacy and safety of corticosteroids in the pediatric population are based on the well-established course of effect of corticosteroids which is similar in pediatric and adult populations. Published studies provide evidence of efficacy and safety in pediatric patients for the treatment of nephrotic syndrome (>2 years of age), and aggressive lymphomas and leukemias (>1 month of age). Other indications for pediatric use of corticosteroids, e.g., severe asthma and wheezing, are based on adequate and well-controlled trials conducted in adults, on the premises that the course of the diseases and their pathophysiology are considered to be substantially similar in both populations.

The adverse effects of corticosteroids in pediatric patients are similar to those in adults (see ADVERSE REACTIONS). Like adults, pediatric patients should be carefully observed with frequent measurements of blood pressure, weight, height, intraocular pressure, and clinical evaluation for the presence of infection, psychosocial disturbances, thromboembolism, peptic ulcers, cataracts, and osteoporosis. Pediatric patients who are treated with corticosteroids by any route, including systemically administered corticosteroids, may experience a decrease in their growth velocity. This negative impact of corticosteroids on growth has been observed at low systemic doses and in the absence of laboratory evidence of HPA axis suppression (i.e., cosyntropin stimulation and basal cortisol plasma levels). Growth velocity may therefore be a more sensitive indicator of systemic corticosteroid exposure in pediatric patients than some commonly used tests of HPA axis function. The linear growth of pediatric patients treated with corticosteroids should be monitored, and the potential growth effects of prolonged treatment should be weighed against clinical benefits obtained and the availability of treatment alternatives. In order to minimize the potential growth effects of corticosteroids, pediatric patients should be titrated to the lowest effective dose.

Geriatric Use

No overall differences in safety or effectiveness were observed between elderly subjects and younger subjects, and other reported clinical experience has not identified differences in responses between the elderly and younger patients, but greater sensitivity of some older individuals cannot be ruled out.

ADVERSE REACTIONS

(listed alphabetically under each subsection)

The following adverse reactions may be associated with corticosteroid therapy:

Allergic reactions: Anaphylaxis including death, and angioedema.

Cardiovascular: Bradycardia, cardiac arrest, cardiac arrhythmias, cardiac enlargement, circulatory collapse, congestive heart failure, fat embolism, hypertension, hypertrophic cardiomyopathy in premature infants, myocardial rupture following recent myocardial infarction (see WARNINGS), pulmonary edema, syncope, tachycardia, thromboembolism, thrombophlebitis, vasculitis.

Dermatologic: Acne, allergic dermatitis, cutaneous and subcutaneous atrophy, dry scaly skin, ecchymoses and petechiae, edema, erythema, hyperpigmentation, hypopigmentation, impaired wound healing, increased sweating, lupus erythematosus-like lesions, purpura, rash, sterile abscess, striae, suppressed reactions to skin tests, thin fragile skin, thinning scalp hair, urticaria.

Endocrine: Decreased carbohydrate and glucose tolerance, development of cushingoid state, glycosuria, hirsutism, hypertrichosis, increased requirements for insulin or oral hypoglycemic agents in diabetes, manifestations of latent diabetes mellitus, menstrual irregularities, postmenopausal vaginal hemorrhage, secondary adrenocortical and pituitary unresponsiveness (particularly in times of stress, as in trauma, surgery, or illness), suppression of growth in pediatric patients.

Fluid and electrolyte disturbances: Congestive heart failure in susceptible patients, fluid retention, hypokalemic alkalosis, potassium loss, sodium retention.

Gastrointestinal: Abdominal distention, bowel/bladder dysfunction (after intrathecal administration [see WARNINGS: Neurologic]), elevation in serum liver enzyme levels (usually reversible upon discontinuation), hepatomegaly, increased appetite, nausea, pancreatitis, peptic ulcer with possible perforation and hemorrhage, perforation of the small and large intestine (particularly in patients with inflammatory bowel disease), ulcerative esophagitis.

Metabolic: Negative nitrogen balance due to protein catabolism.

Musculoskeletal: Aseptic necrosis of femoral and humeral heads, calcinosis (following intra-articular or intralesional use), Charcot-like arthropathy, loss of muscle mass, muscle weakness, osteoporosis, pathologic fracture of long bones, post injection flare (following intra-articular use), steroid myopathy, tendon rupture, vertebral compression fractures.

Neurologic/Psychiatric: Convulsions, depression, emotional instability, euphoria, headache, increased intracranial pressure with papilledema (pseudotumor cerebri) usually following discontinuation of treatment, insomnia, mood swings, neuritis, neuropathy, paresthesia, personality changes, psychiatric disorders, vertigo. Arachnoiditis, meningitis, paraparesis/paraplegia, and sensory disturbances have occurred after intrathecal administration. Spinal cord infarction, paraplegia, quadriplegia, cortical blindness, and stroke (including brainstem) have been reported after epidural administration of corticosteroids (see WARNINGS: Serious Neurologic Adverse Reactions with Epidural Administration and WARNINGS: Neurologic).

Ophthalmic: Exophthalmos, glaucoma, increased intraocular pressure, posterior subcapsular cataracts, rare instances of blindness associated with periocular injections.

Other: Abnormal fat deposits, decreased resistance to infection, hiccups, increased or decreased motility and number of spermatozoa, malaise, moon face, weight gain.

OVERDOSAGE

Treatment of acute overdosage is by supportive and symptomatic therapy. For chronic overdosage in the face of severe disease requiring continuous steroid therapy, the dosage of the corticosteroid may be reduced only temporarily, or alternate day treatment may be introduced.

DOSAGE AND ADMINISTRATION

General

NOTE: CONTAINS BENZYL ALCOHOL (see PRECAUTIONS).

IT SHOULD BE EMPHASIZED THAT DOSAGE REQUIREMENTS ARE VARIABLE AND MUST BE INDIVIDUALIZED ON THE BASIS OF THE DISEASE UNDER TREATMENT AND THE RESPONSE OF THE PATIENT. After a favorable response is noted, the proper maintenance dosage should be determined by decreasing the initial drug dosage in small decrements at appropriate time intervals until the lowest dosage which will maintain an adequate clinical response is reached. Situations which may make dosage adjustments necessary are changes in clinical status secondary to remissions or exacerbations in the disease process, the patient’s individual drug responsiveness, and the effect of patient exposure to stressful situations not directly related to the disease entity under treatment. In this latter situation it may be necessary to increase the dosage of the corticosteroid for a period of time consistent with the patient’s condition. If after long-term therapy the drug is to be stopped, it is recommended that it be withdrawn gradually rather than abruptly.

In pediatric patients, the initial dose of triamcinolone may vary depending on the specific disease entity being treated. The range of initial doses is 0.11 to 1.6 mg/kg/day in 3 or 4 divided doses (3.2 to 48 mg/m^2bsa/day).

For the purpose of comparison, the following is the equivalent milligram dosage of the various glucocorticoids:

Cortisone, 25 | Triamcinolone, 4
Hydrocortisone, 20 | Paramethasone, 2
Prednisolone, 5 | Betamethasone, 0.75
Prednisone, 5 | Dexamethasone, 0.75
Methylprednisolone, 4

These dose relationships apply only to oral or intravenous administration of these compounds. When these substances or their derivatives are injected intramuscularly or into joint spaces, their relative properties may be greatly altered.

Intra-Articular Administration

Dosage

The initial dose of KENALOG-10 Injection for intra-articular administration may vary from 2.5 mg to 5 mg for smaller joints and from 5 mg to 15 mg for larger joints, depending on the specific disease entity being treated. Single injections into several joints, up to a total of 20 mg or more, have been given.

Intralesional

For intralesional administration, the initial dose per injection site will vary depending on the specific disease entity and lesion being treated. The site of injection and volume of injection should be carefully considered due to the potential for cutaneous atrophy.

Multiple sites separated by one centimeter or more may be injected, keeping in mind that the greater the total volume employed the more corticosteroid becomes available for systemic absorption and systemic effects. Such injections may be repeated, if necessary, at weekly or less frequent intervals.

Localization of Doses

The lower dosages in the initial dosage range of triamcinolone acetonide may produce the desired effect when the corticosteroid is administered to provide a localized concentration. The site and volume of the injection should be carefully considered when triamcinolone acetonide is administered for this purpose.

Administration

STRICT ASEPTIC TECHNIQUE IS MANDATORY. The vial should be shaken before use to ensure a uniform suspension. Prior to withdrawal, the suspension should be inspected for clumping or granular appearance (agglomeration). Agglomeration occurs when the drug substance separates from the solution and appears as a white precipitate in the vial. An agglomerated product should be discarded and should not be used. After withdrawal, inject without delay to prevent settling in the syringe.

Injection Technique

For treatment of joints, the usual intra-articular injection technique should be followed. If an excessive amount of synovial fluid is present in the joint, some, but not all, should be aspirated to aid in the relief of pain and to prevent undue dilution of the steroid.

With intra-articular administration, prior use of a local anesthetic may often be desirable. Care should be taken with this kind of injection, particularly in the deltoid region, to avoid injecting the suspension into the tissues surrounding the site, since this may lead to tissue atrophy.

In treating acute nonspecific tenosynovitis, care should be taken to ensure that the injection of KENALOG-10 Injection is made into the tendon sheath rather than the tendon substance. Epicondylitis may be treated by infiltrating the preparation into the area of greatest tenderness.

Intralesional

For treatment of dermal lesions, KENALOG-10 Injection should be injected directly into the lesion, i.e., intradermally or subcutaneously. For accuracy of dosage measurement and ease of administration, it is preferable to employ a tuberculin syringe and a small-bore needle (23-25 gauge). Ethyl chloride spray may be used to alleviate the discomfort of the injection.

HOW SUPPLIED

KENALOG®-10 Injection (triamcinolone acetonide injectable suspension, USP) is supplied in 5 mL multiple-dose vials (NDC 0003-0494-20) providing 10 mg triamcinolone acetonide per mL.

Storage

Store at controlled room temperature, 20°C to 25°C (68°F to 77°F); protect from temperatures below 20°C (68°F). Excursions are permitted between 15°C and 30°C (59°F and 86°F). Store vial in carton to protect from light. Do not refrigerate. Store vial upright.

Once in use: Chemical and physical in-use stability has been demonstrated for 28 days below 25°C (77°F).

From a microbiological point of view, once opened, the product may be stored for a maximum of 28 days at 15°C to 25°C (59°F to 77°F). Other in-use storage times and conditions are the responsibility of the user.

Bristol-Myers Squibb Company
Princeton, NJ 08543 USA

Revised: Aug 2024

KENALOG-10 50 mg per 5 mL Injectable Suspension Representative Packaging

See How Supplied section for a complete list of available packages of KENALOG-10.

NDC 0003-0494-20
Rx only
KENALOG®-10
(Triamcinolone Acetonide
Injectable Suspension, USP)
50 mg per 5 mL
5 mL Multiple-Dose Vial